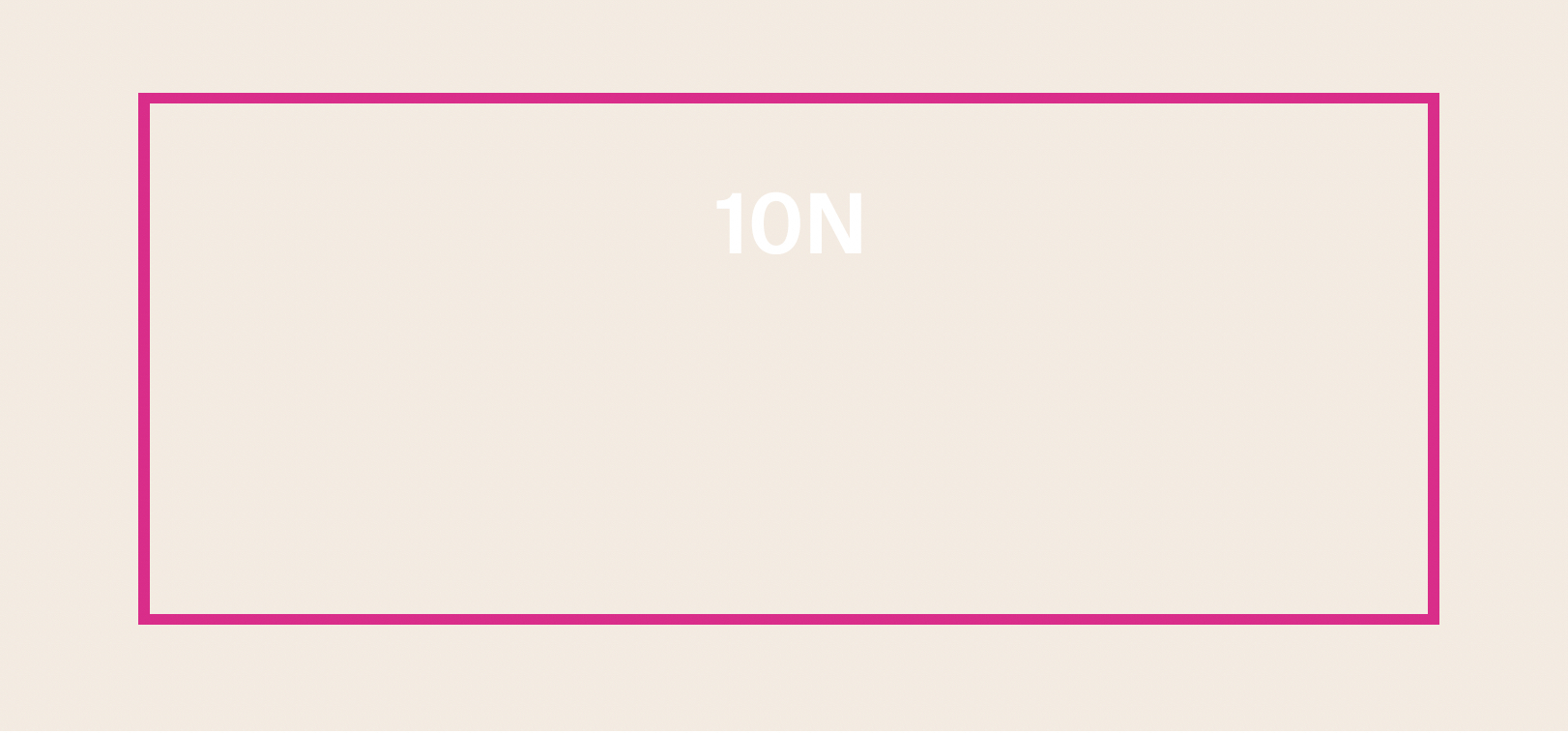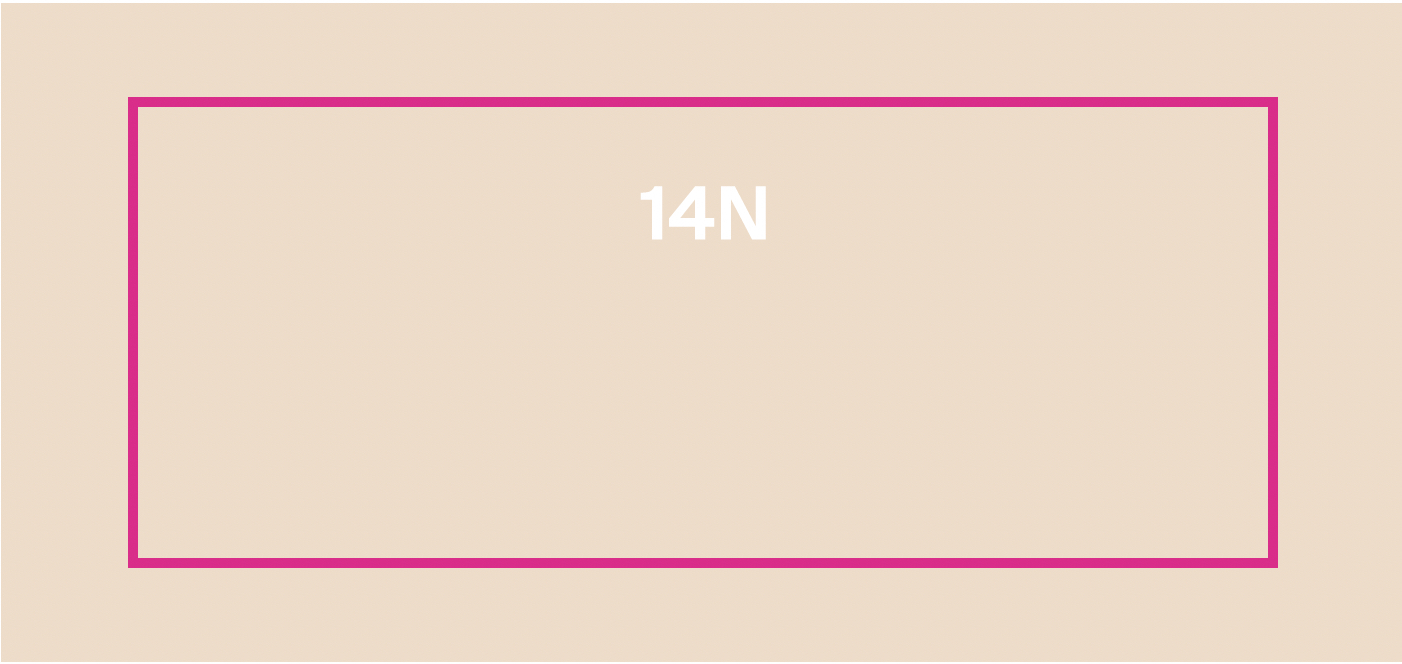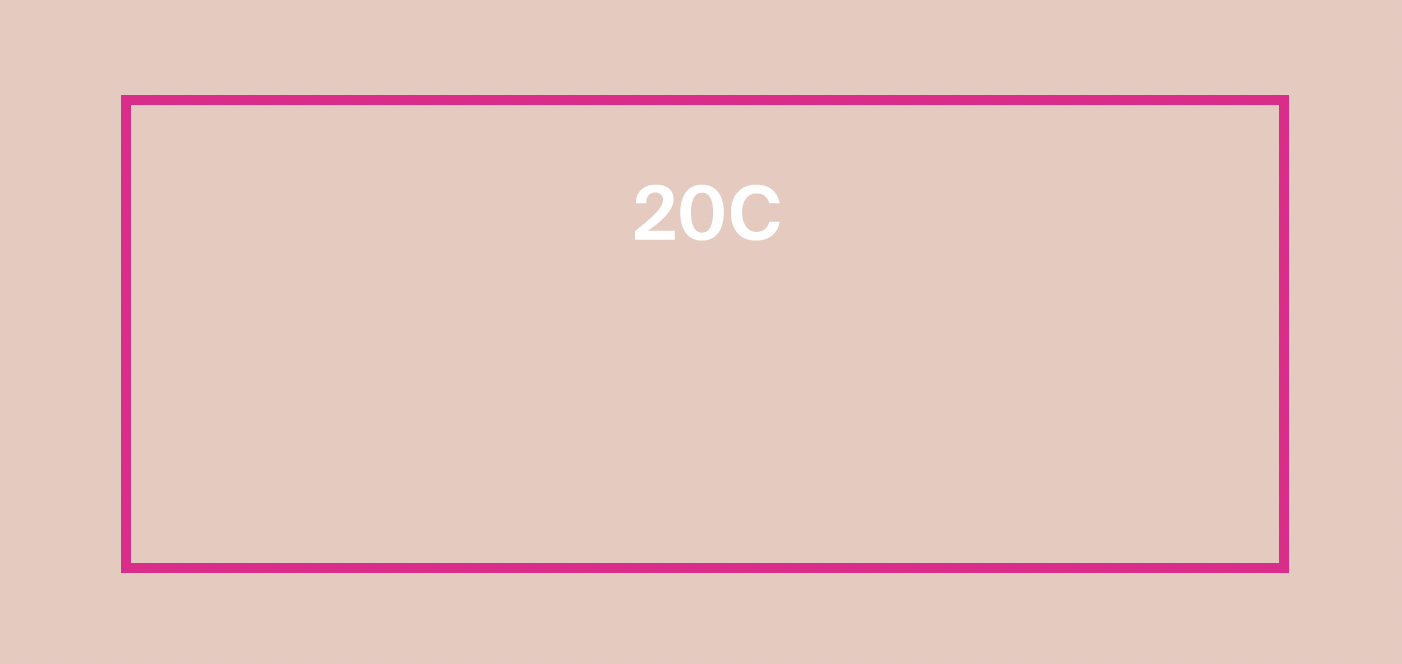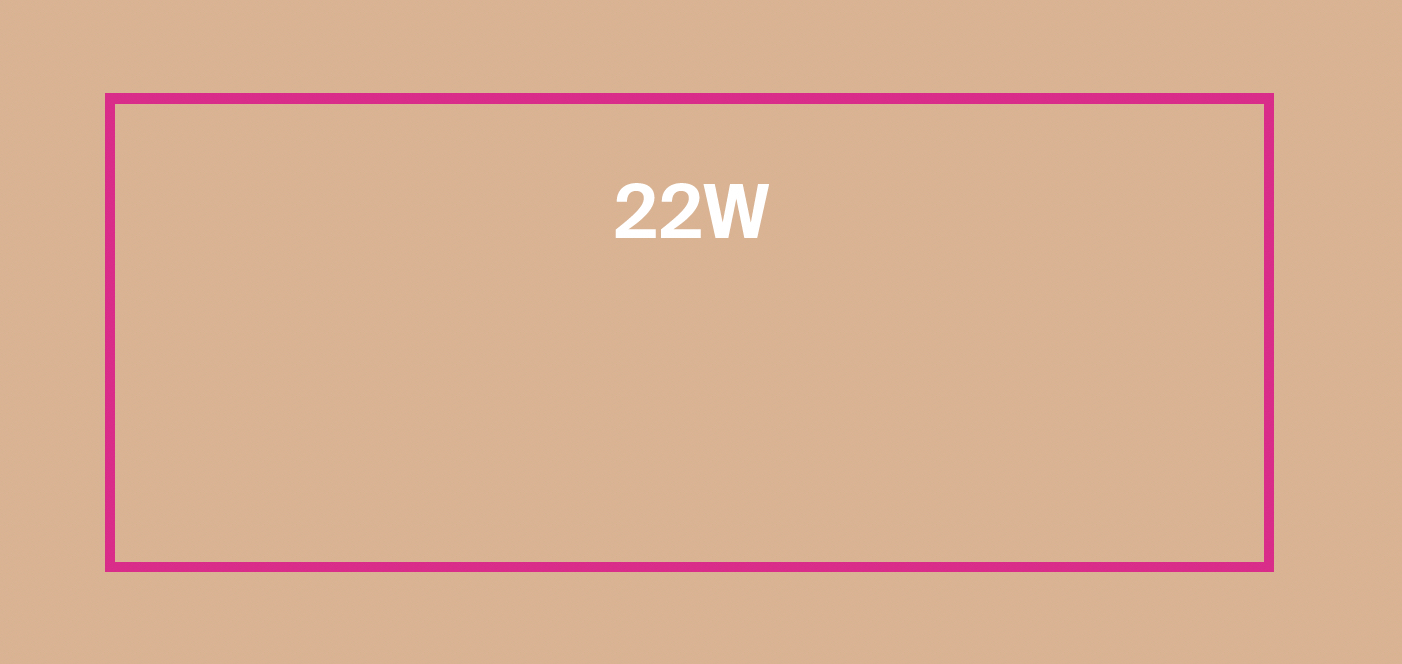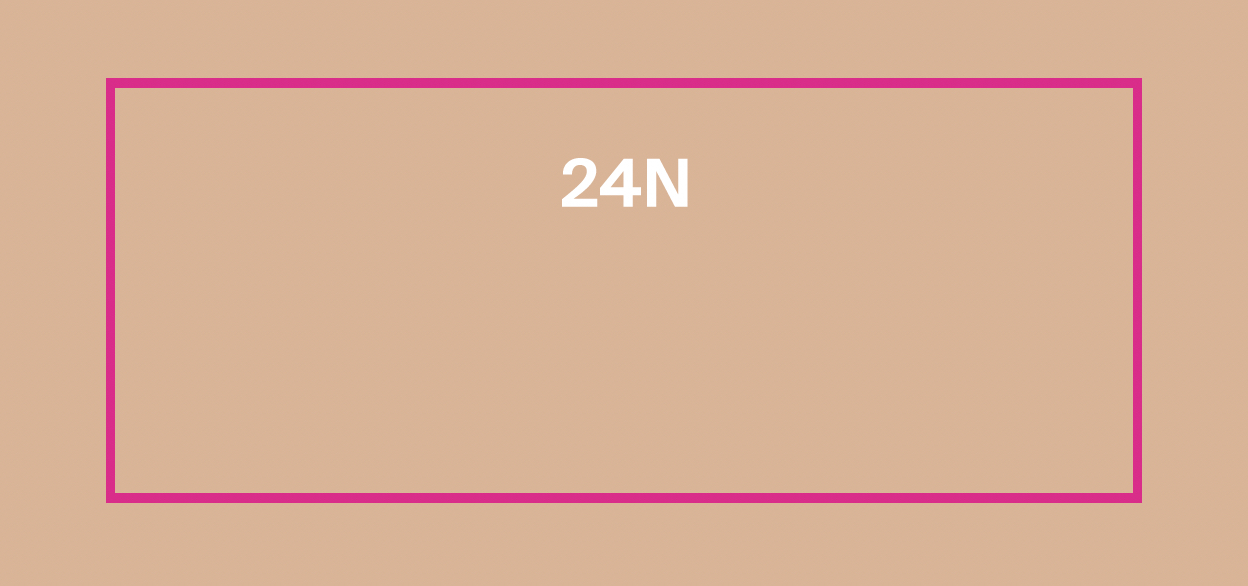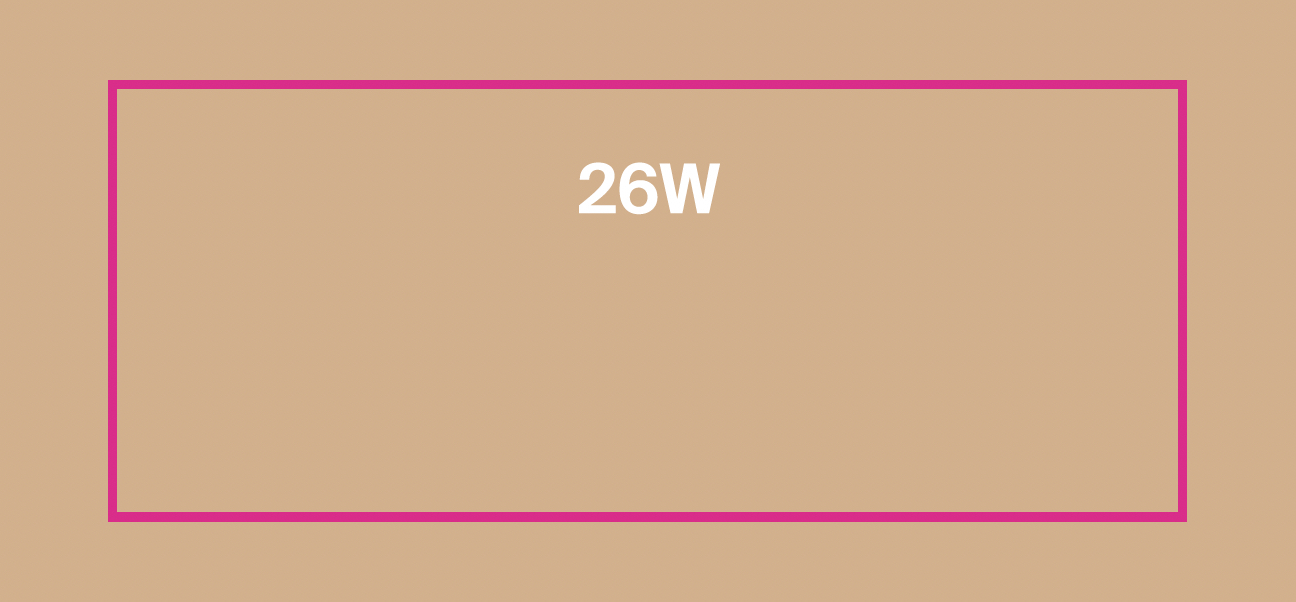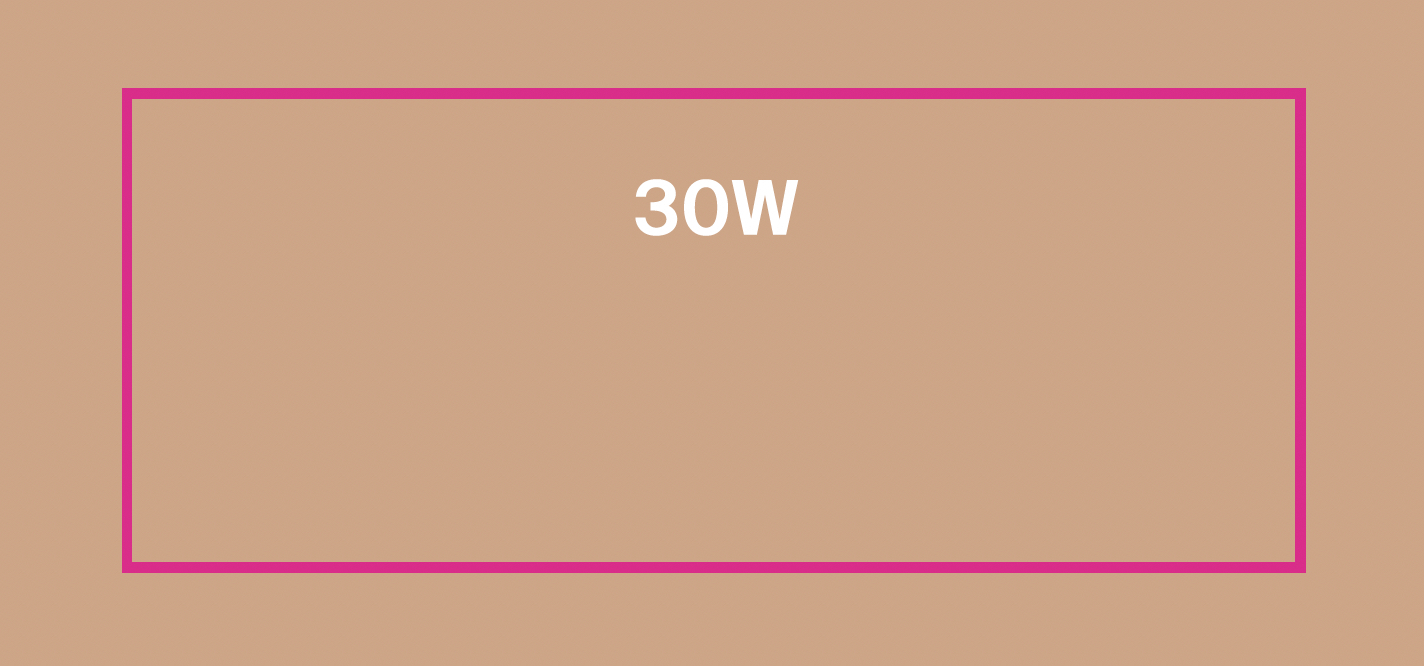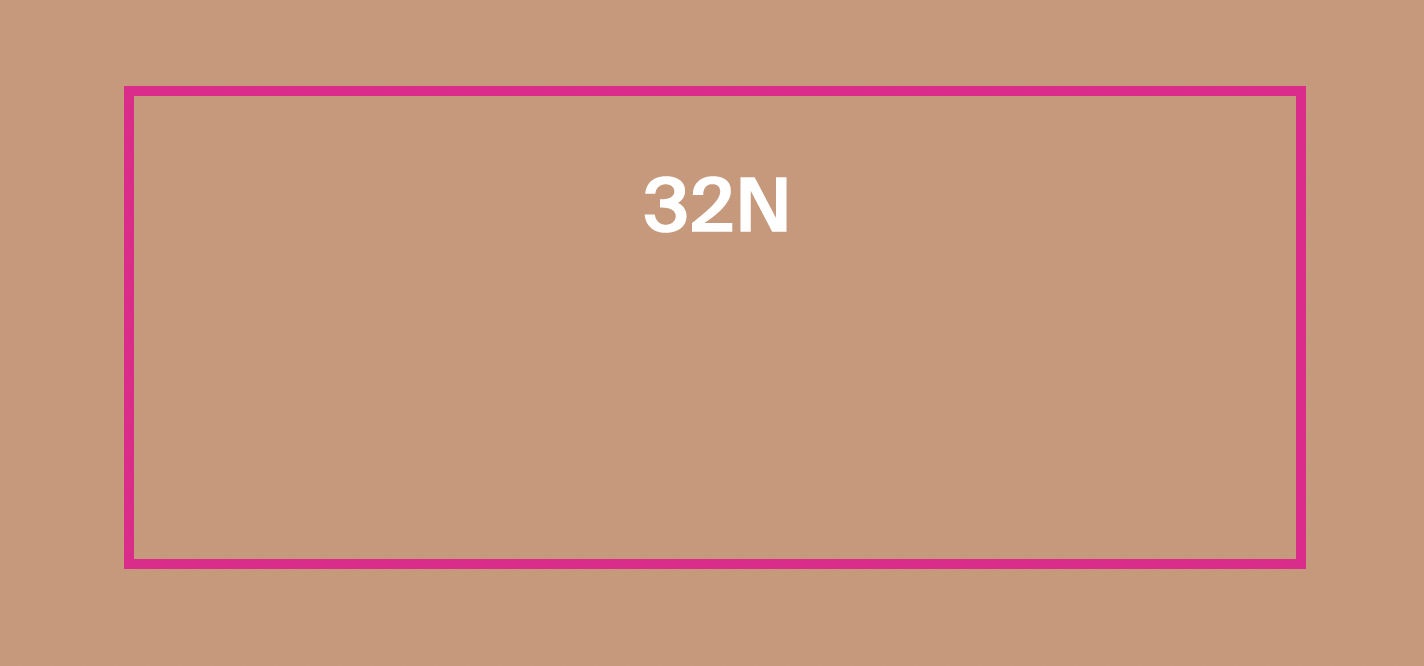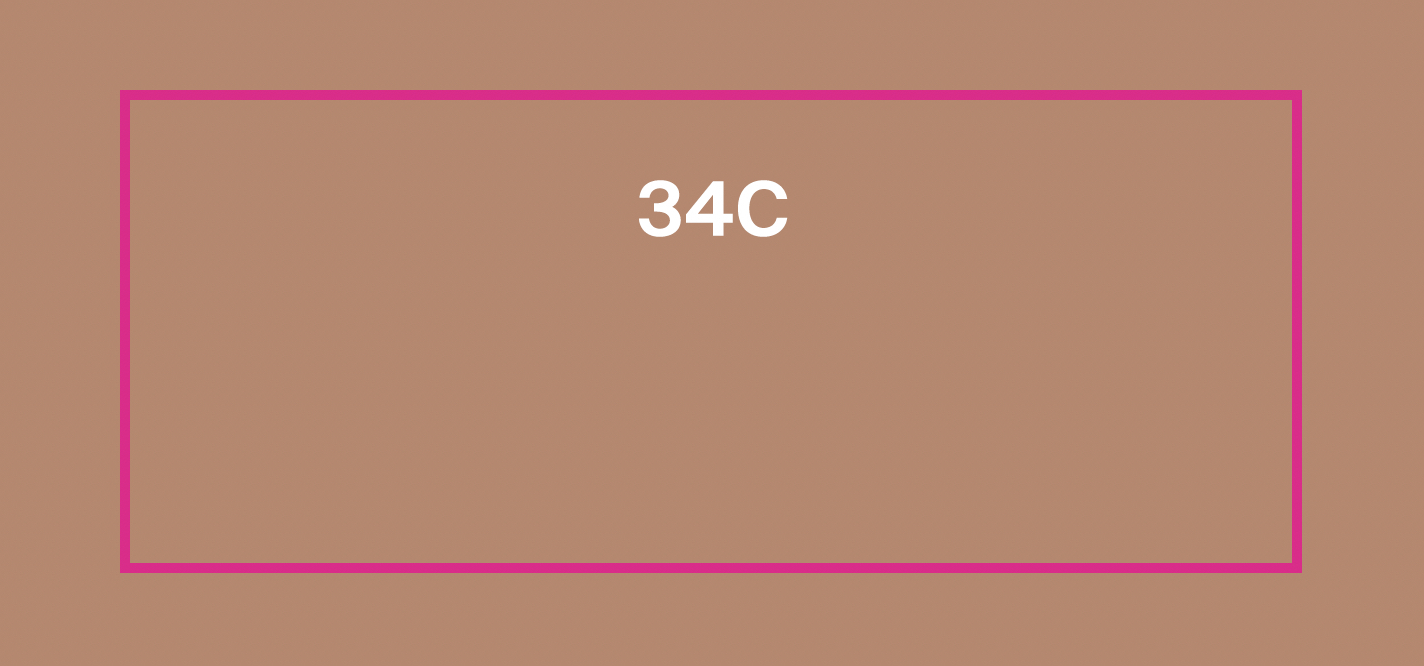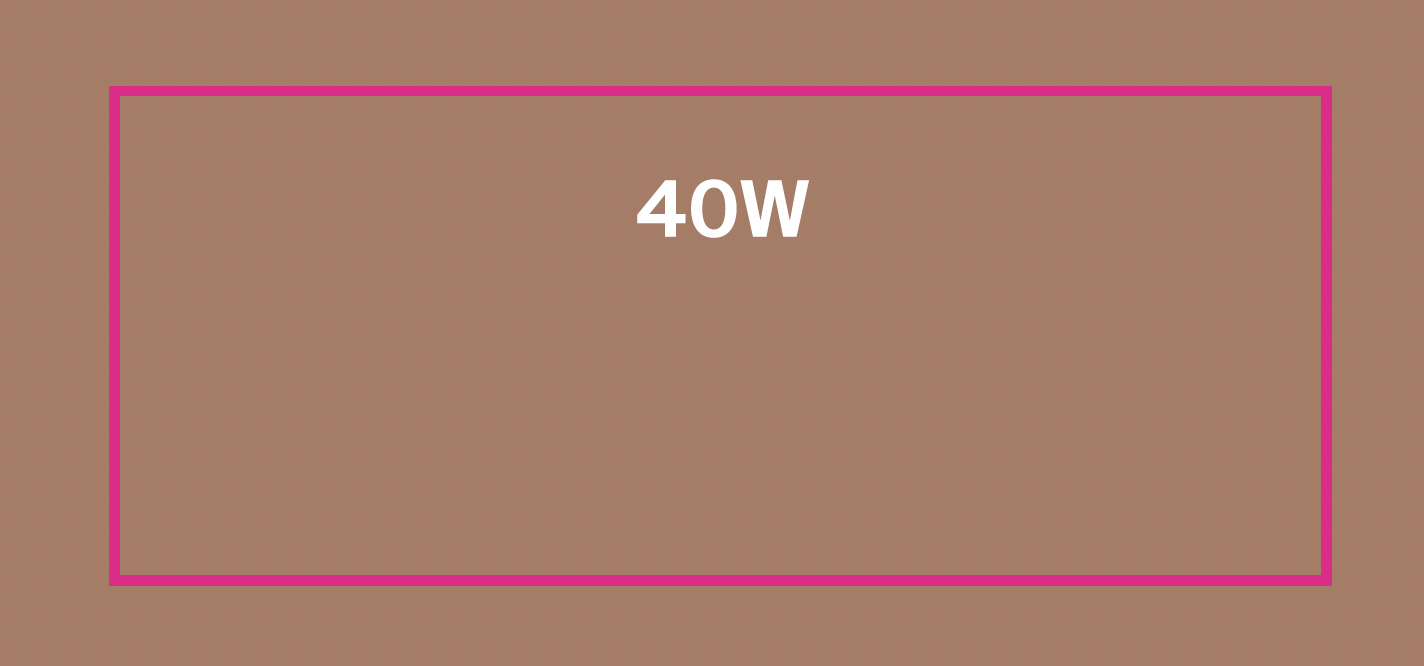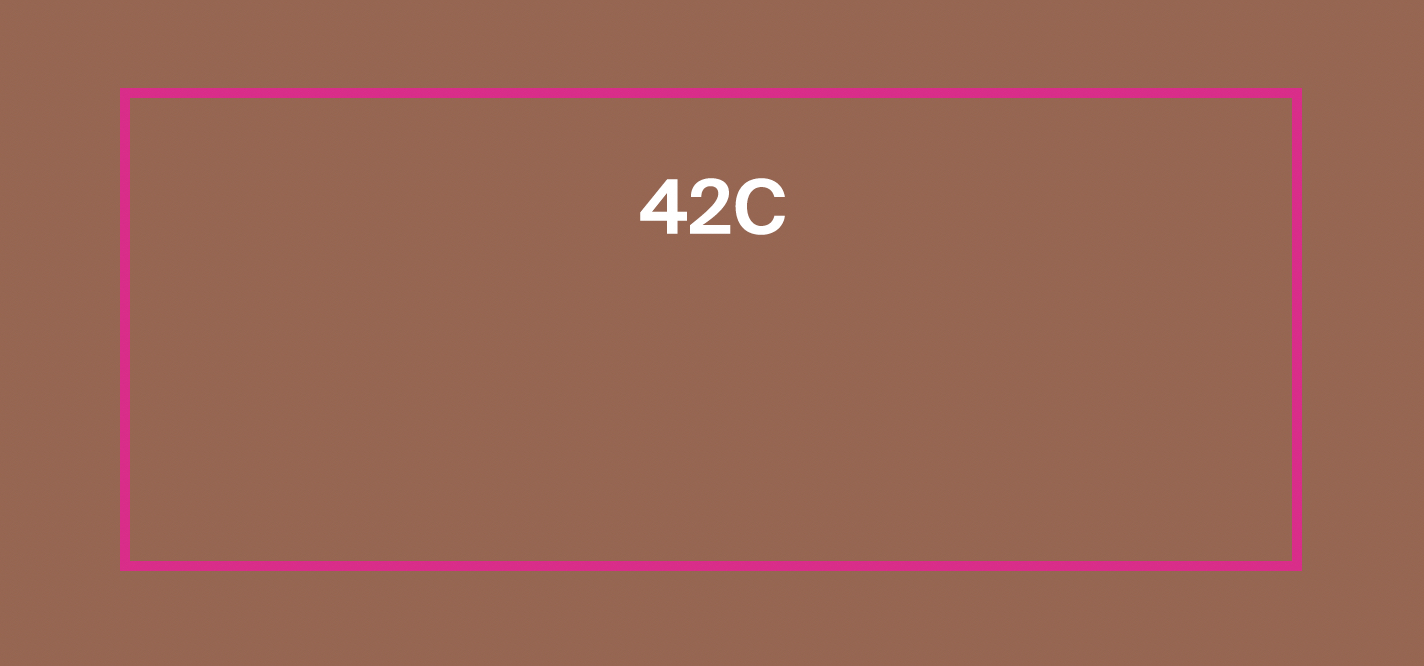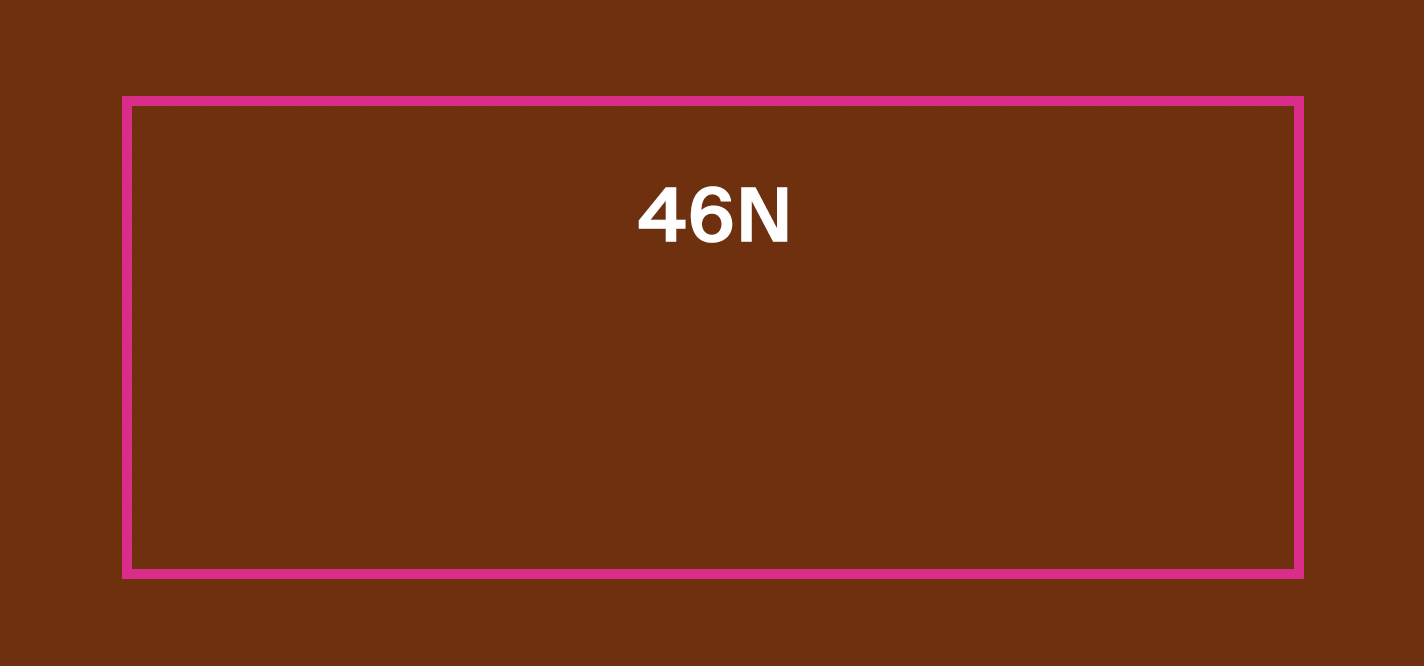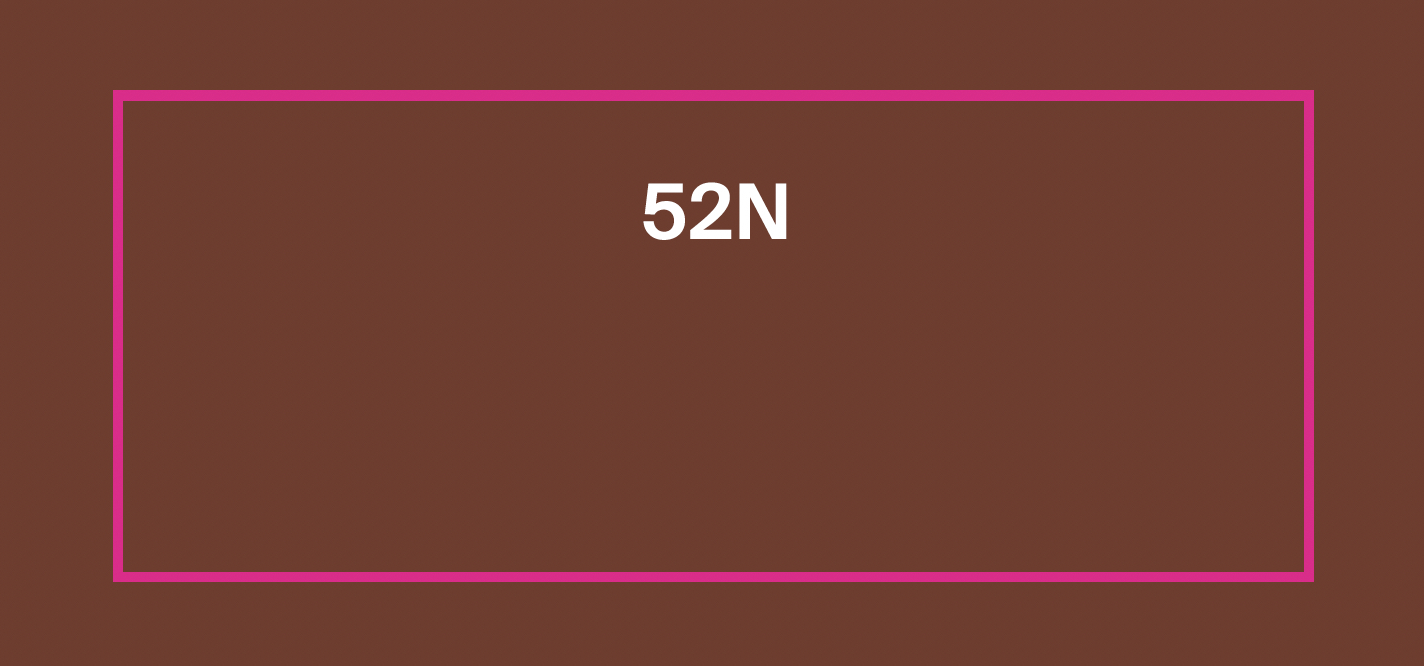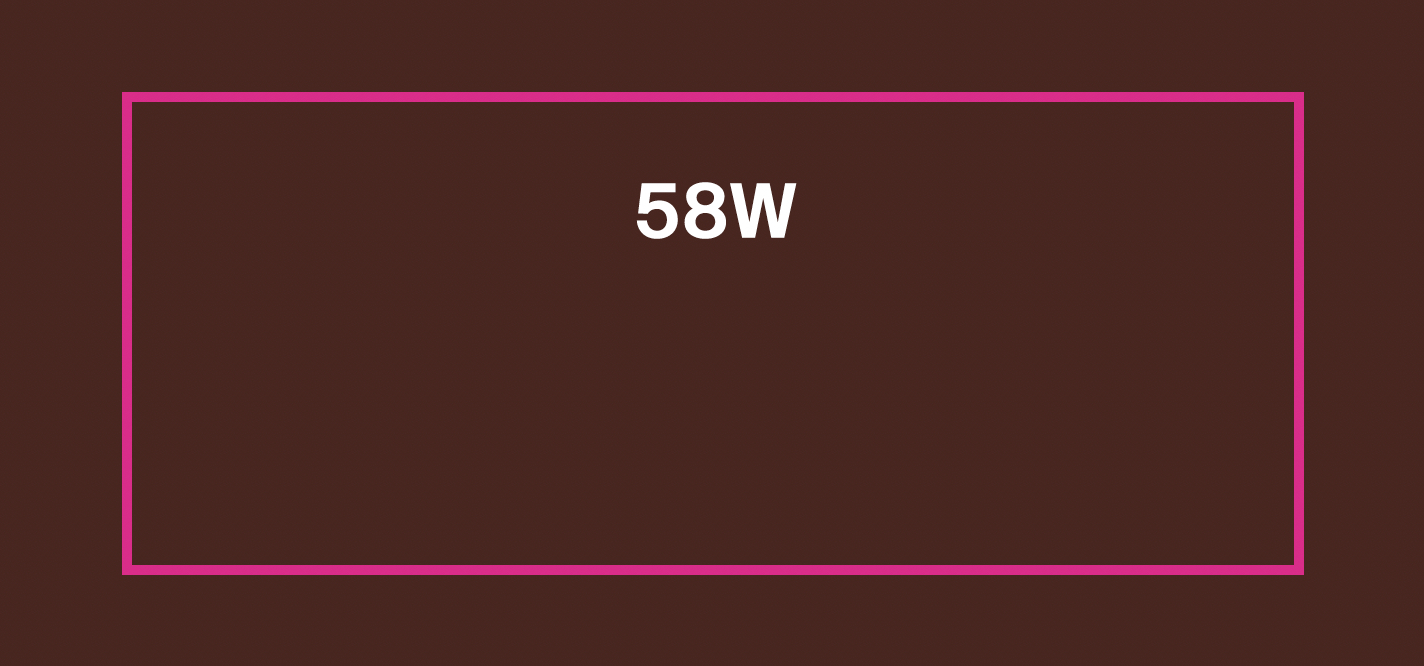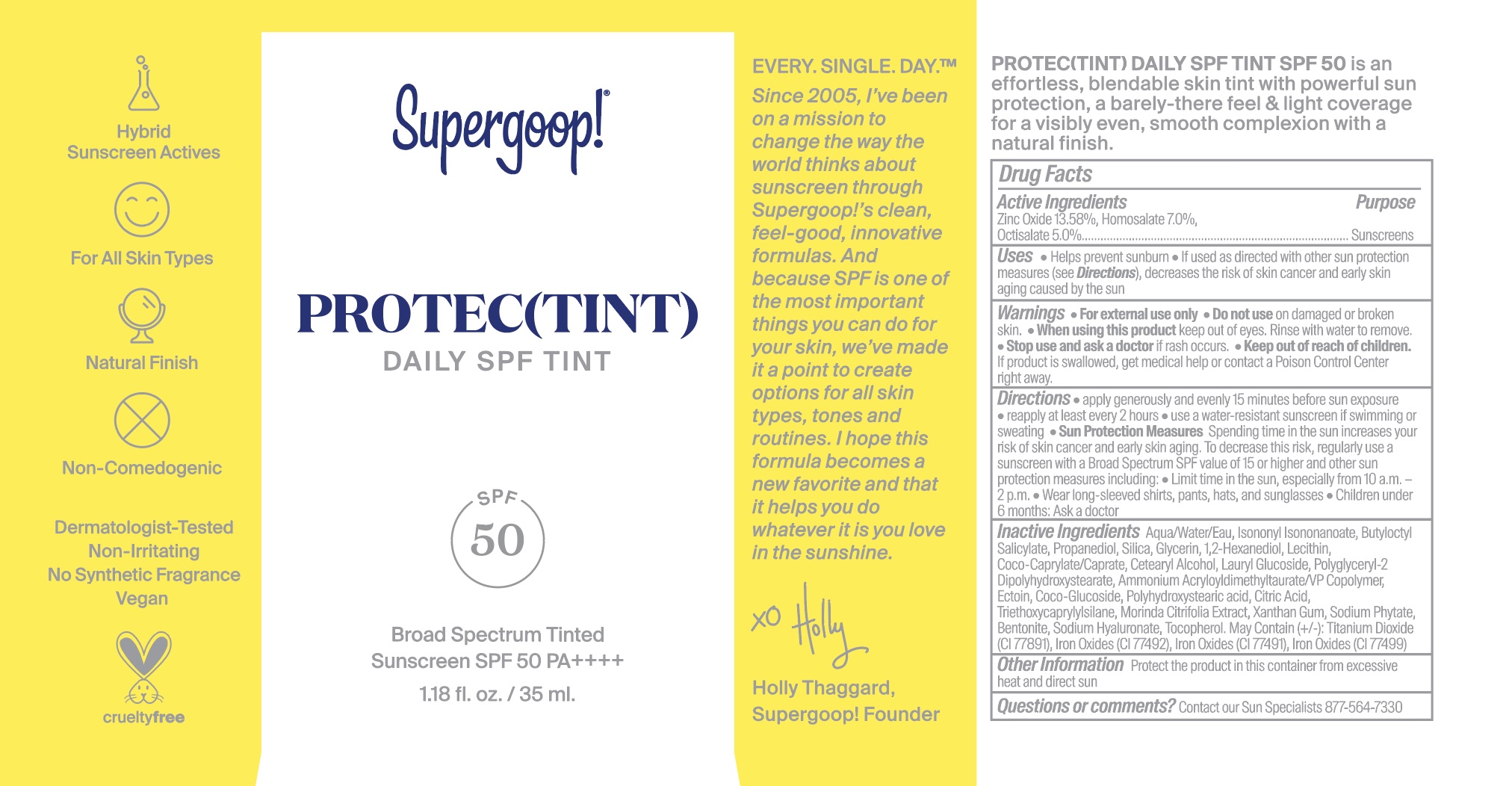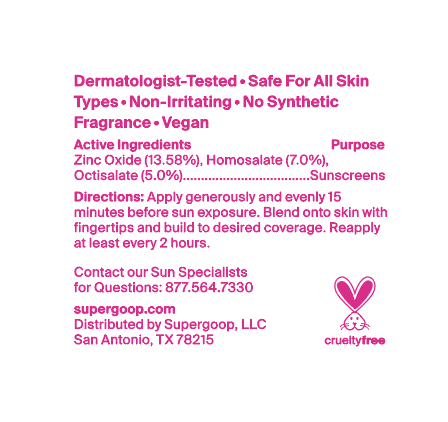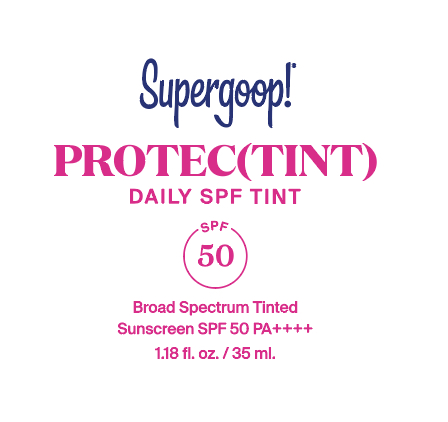 DRUG LABEL: ProtecTINT 20C
NDC: 75936-625 | Form: CREAM
Manufacturer: Supergoop, LLC
Category: otc | Type: HUMAN OTC DRUG LABEL
Date: 20251007

ACTIVE INGREDIENTS: HOMOSALATE 7 g/100 mL; ZINC OXIDE 13.58 g/100 mL; OCTISALATE 5 g/100 mL
INACTIVE INGREDIENTS: TOCOPHEROL; FERRIC OXIDE YELLOW; FERRIC OXIDE RED; ISONONYL ISONONANOATE; GLYCERIN; NONI FRUIT; PHYTATE SODIUM; FERROSOFERRIC OXIDE; POLYHYDROXYSTEARIC ACID (2300 MW); XANTHAN GUM; HYALURONATE SODIUM; TITANIUM DIOXIDE; PROPANEDIOL; CETOSTEARYL ALCOHOL; LAURYL GLUCOSIDE; POLYGLYCERYL-2 DIPOLYHYDROXYSTEARATE; AMMONIUM ACRYLOYLDIMETHYLTAURATE/VP COPOLYMER; COCO GLUCOSIDE; WATER; 1,2-HEXANEDIOL; LECITHIN, SUNFLOWER; COCO-CAPRYLATE/CAPRATE; TRIETHOXYCAPRYLYLSILANE; BENTONITE; BUTYLOCTYL SALICYLATE; SILICON DIOXIDE; ECTOINE; CITRIC ACID MONOHYDRATE

Protec(tint) SPF 50

ACTIVE INGREDIENT

Active Ingredients: Zinc Oxide 13.58%, Homosalate 7.0%, Octisalate 5.0%

PURPOSE

Helps prevent sunburn

If used as directed with other sun protection measures (see Directions), decreases the risk of skin cancer and early skin aging caused by the sun

Keep out of reach of children. If product is swallowed, get medical help, or contact a poison control center right away.

WARNINGS

For External use only

Do not use on damaged or broken skin

When using this product, keep out of eyes. Rinse with water to remove

Stop use and ask a doctor if rash occurs

Directions

Apply generously and evenly 15 minutes before sun exposure

Reapply at least every 2 hours

Use a water resistant sunscreen if swimming or sweating

Sun Protection Measures: Spending time in the sun increases your risk of skin cancer and early skin aging. To decrease this risk, regularly use a sunscreen with a Broad Spectrum SPF value of 15 or higher and other sun protection measures including:

- Limit time in the sun, especially from 10 a.m.- 2 p.m.
- Wear long-sleeved shirts, pants, hats, and sunglasses
- Children under 6 months: Ask a doctor

INACTIVE INGREDIENT

Inactive Ingredients:IAqua/Water/Eau, Isononyl Isononanoate, Butyloctyl Salicylate, Propanediol, Silica, Glycerin,1,2-Hexanediol, Lecithin, Coco-Caprylate/Caprate, Cetearyl Alcohol, Lauryl Glucoside, Polyglyceryl-2 Dipolyhydroxystearate, Ammonium Acryloyldimethyltaurate/VP Copolymer, Ectoin, Coco-Glucoside, Polyhydroxystearic acid, Citric Acid, Triethoxycaprylylsilane, Morinda Citrifolia Extract, Xanthan Gum, Sodium Phytate, Bentonite, Sodium Hyaluronate, Tocopherol

PACKAGE LABEL

Protec(tint)

Daily SPF Tint

SPF 50

Broad Spectrum Tinted

Sunscreen SPF 50

1.18 fl. oz. / 35 ml.

SHADE LABELS